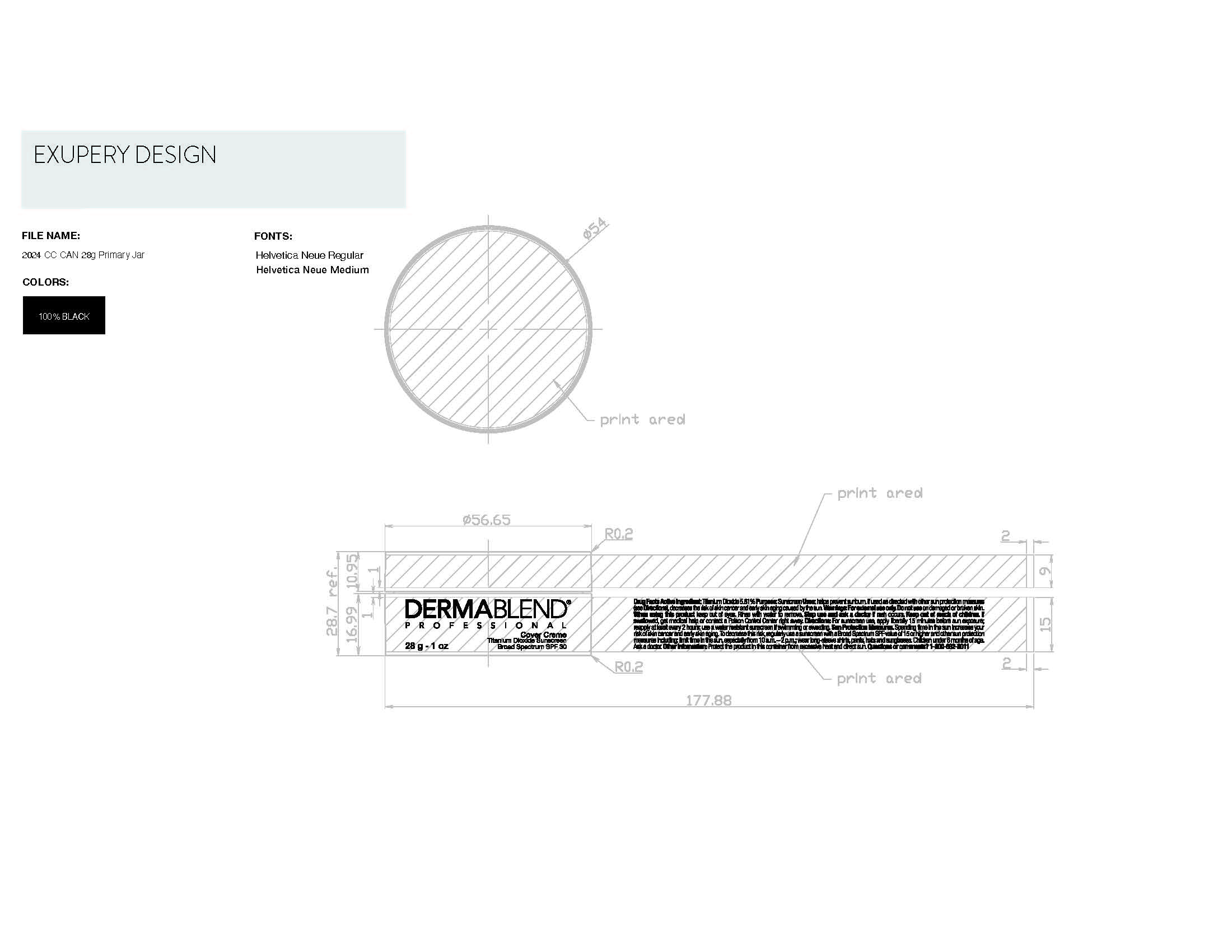 DRUG LABEL: Cover Creme
NDC: 84203-005 | Form: CREAM
Manufacturer: Baxter of California
Category: otc | Type: HUMAN OTC DRUG LABEL
Date: 20250404

ACTIVE INGREDIENTS: TITANIUM DIOXIDE 30 mg/1 g
INACTIVE INGREDIENTS: MINERAL OIL; KAOLIN; BARIUM SULFATE; MAGNESIUM CARBONATE; CARNAUBA WAX; STEARIC ACID; PHENOXYETHANOL; TRIETHOXYCAPRYLYLSILANE; CAPRYLYL GLYCOL; LAUROYL LYSINE; ALLANTOIN; SILICA DIMETHYL SILYLATE; ALUMINUM HYDROXIDE; MICROCRYSTALLINE WAX; MODIFIED CORN STARCH (1-OCTENYL SUCCINIC ANHYDRIDE); ISOPROPYL PALMITATE; TOCOPHEROL; SYNTHETIC BEESWAX

Dermablend Professional cover creme

Active Ingredient

Titanium Dioxide 5.81%

Purpose

Sunscreen

Uses

helps prevent sunburn. If used as directed with other sun protection measures (see Directions), decreases the risk of skin cancer and early skin aging caused by the sun.

For external use only

Do not use on damaged or broken skin.

When using this product keep out of eyes. Rinse with water to remove.

Stop use and ask a doctor if rash occurs.

Keep out of reach of children

If swallowed, get medical help or contact a Poison Control Cneter right away.

Directions

For sunscreen use, apply liberally 15 minutes before sun exposure; reapply at least every 2 hours; use a water resistant sunscreen if swimming or sweating.

Sun Protection Measures

Spending time n the sun increases your risk of skin cancer and early skin aging. To decrease this risk, regularly use a sunscreen with a Broad Spectrun SPF value of 15 or higher and other sun protection measures including; limit time in the sun, especially from 10a.m.-2p.m.; wear long-sleeve shirts, pants, hats and sunglasses. Children under 6 months of age. Ask a doctor.

Other information

Protect the product in this container from excessive heat and direct sun

Inactive ingredients

mineral oil (paraffinum liquidum), zea mays (corn) starch, synthetic beeswax, kaolin, barium sulfate, isopropyl plamitate, magnesium carbonate, copernicia cerifera (carnauba) wax, aluminum hydroxide, microcrystalline wax (cera microcristallina), stearic acid, phenoxyethanol, triethoxycaprylylsilane, caprylyl glycol, lauroyl lysine, allantoin, silica silylate, tocopherol. may contain: iron oxides, titanium dioxide

Questions or comments?

1-800-662-8011